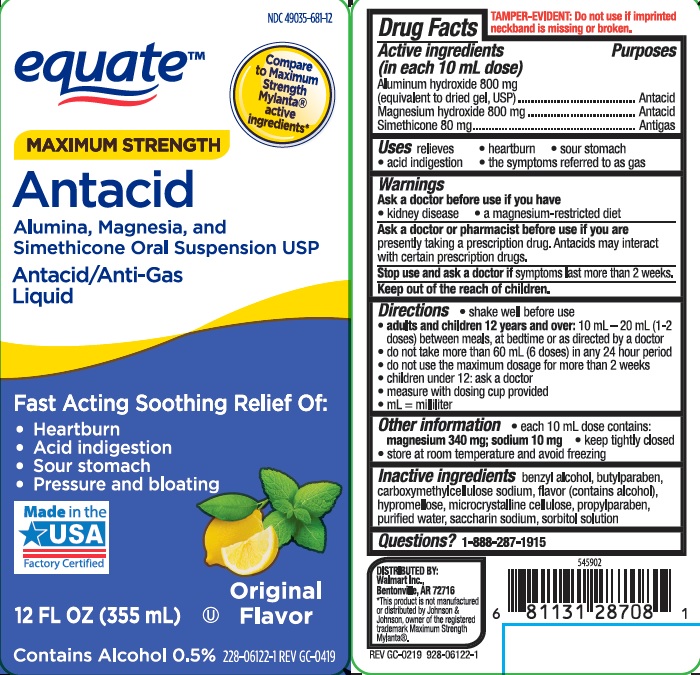 DRUG LABEL: MAXIMUM STRENGTH ANTACID
NDC: 49035-681 | Form: SUSPENSION
Manufacturer: WAL-MART STORES, INC.
Category: otc | Type: HUMAN OTC DRUG LABEL
Date: 20231101

ACTIVE INGREDIENTS: ALUMINUM HYDROXIDE 800 mg/10 mL; MAGNESIUM HYDROXIDE 800 mg/10 mL; DIMETHICONE 80 mg/10 mL
INACTIVE INGREDIENTS: SORBITOL; BENZYL ALCOHOL; BUTYLPARABEN; CARBOXYMETHYLCELLULOSE SODIUM; HYPROMELLOSES; CELLULOSE, MICROCRYSTALLINE; PROPYLPARABEN; WATER; SACCHARIN SODIUM

walmart ant max

Active ingredients (in each 10 mL dose)

Aluminum hydroxide 800 mg (equivalent to dried gel, USP)

Magnesium hydroxide 800 mg

Simethicone 80mg

Purposes

Antacid

Antigas

Uses

relieves

- heartburn
- sour stomach
- acid indigestion
- the symptoms referred to as gas

Warnings

Ask a doctor before use if you have

• kidney disease

• a magnesium-restricted diet

Ask a doctor or pharmacist before use if you are taking a prescription drug.

Antacids may interact with certain prescription drugs.

Stop use and ask a doctor if symptoms last more than 2 weeks

Keep out of the reach of children.

Directions

- shake well before use
- adults and children 12 years and over: 10 mL-20 mL (1-2 doses) between meals, at bedtime, or as directed by a doctor
- do not take more than 60 mL (6 doses) in any 24 hour period
- do not use the maximum dosage for more than 2 weeks
- children under 12 years: ask a doctor
- measure with dosing cup provided
- mL=milliliter

Other information

- each 10 mL dose contains: magnesium 340 mg; sodium 10 mg
- keep tightly closed
- store at room temperature and avoid freezing

Inactive ingredients

benzyl alcohol, butylparaben, carboxymethylcellulose sodium, flavor (contains alcohol), hypromellose, microcrystalline cellulose, propylparaben, purified water, saccharin sodium, sorbitol solution

Questions or comments?

1-888-287-1915